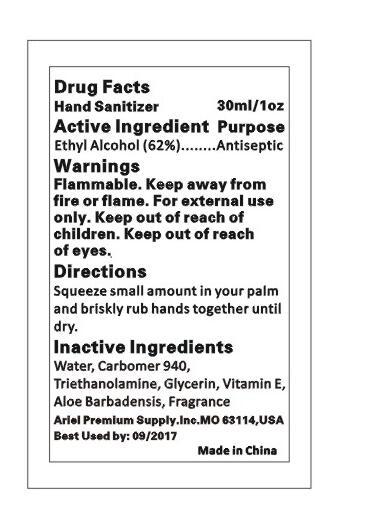 DRUG LABEL: HAND SANITIZER
NDC: 47993-203 | Form: LIQUID
Manufacturer: NINGBO JIANGBEI OCEAN STAR TRADING CO.,LTD
Category: otc | Type: HUMAN OTC DRUG LABEL
Date: 20200422

ACTIVE INGREDIENTS: ALCOHOL 62 g/100 g
INACTIVE INGREDIENTS: CARBOMER 940 12 g/100 g; TRIETHANOLAMINE BENZOATE 3 g/100 g; ALOE VERA LEAF 1 g/100 g; TOCOPHEROL 0.5 g/100 g; AROMADENDRIN 0.2 g/100 g; WATER 19.3 g/100 g; GLYCERIN 2 g/100 g

47993-203

Active ingredients--------------purpose

Ethyl Alcohol 62%------------antiseptic

Uses:
Reduces bacteria on the skin. Recommended for repeated use.

Warnings:

Flammable:Keep away from fire or flame.For external use only.Keep out of reach of choldren.Keep out of reach of eyes.

Directions:

Squeeze small amount in your palm and briskly rub hands together until dry.

Other Information

Do not store above 110F(43C) May discolor certain fabric or surfaces. Harmful to wood finishes and plastics.

KEEP OUT OF REACH OF CHILDREN

Children under 6 years of age should be super vised when using this product.

Inactive Ingredients:

Water,Carbomer 940,Triethanolamine,Glycerin,Vitamin E,Aloe Barbadensis,Fragrance